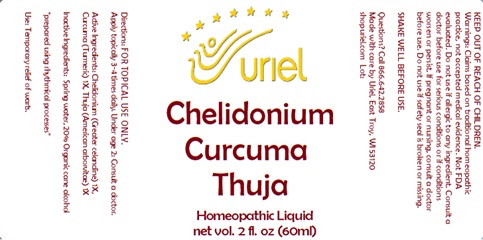 DRUG LABEL: Chelidonium Curcuma Thuja
NDC: 48951-3078 | Form: LIQUID
Manufacturer: Uriel Pharmacy Inc.
Category: homeopathic | Type: HUMAN OTC DRUG LABEL
Date: 20240426

ACTIVE INGREDIENTS: CHELIDONIUM MAJUS ROOT 1 [hp_X]/1 mL; TURMERIC 1 [hp_X]/1 mL; THUJA OCCIDENTALIS WHOLE 1 [hp_X]/1 mL
INACTIVE INGREDIENTS: WATER; ALCOHOL

Chelidonium Curcuma Thuja

INDICATIONS AND USAGE

Directions: FOR TOPICAL USE ONLY.

DOSAGE AND ADMINISTRATION

Apply topically 3-4 times daily. Under age 2: Consult a doctor.

ACTIVE INGREDIENT

Active Ingredients: Chelidonium (Greater celandine) 1X, Curcuma (Turmeric) 1X, Thuja (American arborvitae) 1X

Inactive Ingredients: Distilled water, 20% Organic cane alcohol

"prepared using rhythmical processes"

PURPOSE

Use: Temporary relief of warts.

KEEP OUT OF REACH OF CHILDREN.

Warnings: FOR EXTERNAL USE ONLY.
Claims based on traditional homeopathic practice, not accepted medical evidence. Not FDA evaluated. Do not use if allergic to any ingredient. Consult a doctor before use for serious conditions, if conditions worsen or persist, or accidental ingestion occurs. If pregnant or nursing, consult a doctor before use. Do not use if safety seal is broken or missing. Shake Well Before Use.

QUESTIONS

Questions? Call 866.642.2858 Made with care by Uriel, East Troy, WI 53120 shopuriel.com Lot: